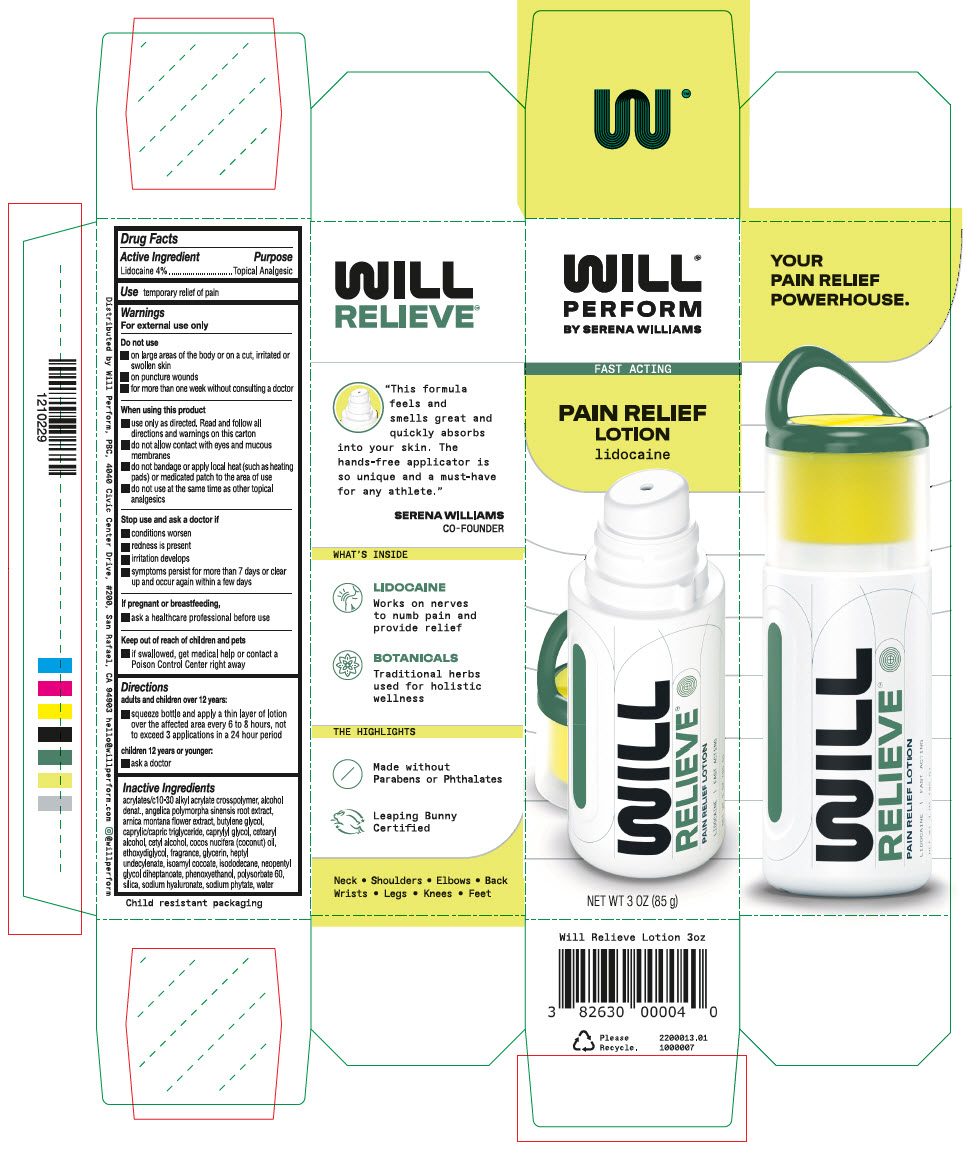 DRUG LABEL: Will Relieve
NDC: 82630-001 | Form: LOTION
Manufacturer: Will Perform, PBC
Category: otc | Type: HUMAN OTC DRUG LABEL
Date: 20230713

ACTIVE INGREDIENTS: Lidocaine 3.4 g/85 g
INACTIVE INGREDIENTS: CARBOMER COPOLYMER TYPE B (ALLYL PENTAERYTHRITOL CROSSLINKED); Alcohol; ANGELICA SINENSIS ROOT; Arnica Montana Flower; Butylene Glycol; Medium-Chain Triglycerides; CAPRYLYL GLYCOL; CETOSTEARYL ALCOHOL; CETYL ALCOHOL; Coconut Oil; DIETHYLENE GLYCOL MONOETHYL ETHER; Polysorbate 60; Glycerin; HEPTYL UNDECYLENATE; ISOAMYL COCOATE; ISODODECANE; NEOPENTYL GLYCOL DIHEPTANOATE; PHENOXYETHANOL; SILICON DIOXIDE; HYALURONATE SODIUM; PHYTATE SODIUM; Water

Will Relieve™ Lotion

Drug Facts

Active Ingredient

Lidocaine 4%

Purpose

Topical Analgesic

Use

temporary relief of pain

Warnings

For external use only

Do not use

- on large areas of the body or on a cut, irritated or swollen skin
- on puncture wounds
- for more than one week without consulting a doctor

When using this product

- use only as directed. Read and follow all directions and warnings on this carton
- do not allow contact with eyes and mucous membranes
- do not bandage or apply local heat (such as heating pads) or medicated patch to the area of use
- do not use at the same time as other topical analgesics

Stop use and ask a doctor if

- conditions worsen
- redness is present
- irritation develops
- symptoms persist for more than 7 days or clear up and occur again within a few days

PREGNANCY OR BREAST FEEDING

If pregnant or breastfeeding,

- ask a healthcare professional before use

Keep out of reach of children and pets

- if swallowed, get medical help or contact a Poison Control Center right away

Directions

adults and children over 12 years:

- squeeze bottle and apply a thin layer of lotion over the affected area every 6 to 8 hours, not to exceed 3 applications in a 24 hour period

children 12 years or younger:

- ask a doctor

Inactive Ingredients

acrylates/c10-30 alkyl acrylate crosspolymer, alcohol denat., angelica polymorpha sinensis root extract, arnica montana flower extract, butylene glycol, caprylic/capric triglyceride, caprylyl glycol, cetearyl alcohol, cetyl alcohol, cocos nucifera (coconut) oil, ethoxydiglycol, fragrance, glycerin, heptyl undecylenate, isoamyl cocoate, isododecane, neopentyl glycol diheptanoate, phenoxyethanol, polysorbate 60, silica, sodium hyaluronate, sodium phytate, water

Distributed by Will Perform, PBC, 570 Pacific Ave., San Francisco, CA 94133

PRINCIPAL DISPLAY PANEL - 85 g Bottle Carton

WILL™
PERFORM
BY SERENA WILLIAMS

FAST ACTING

PAIN RELIEF
LOTION
lidocaine

NET WT 3 OZ (85 g)